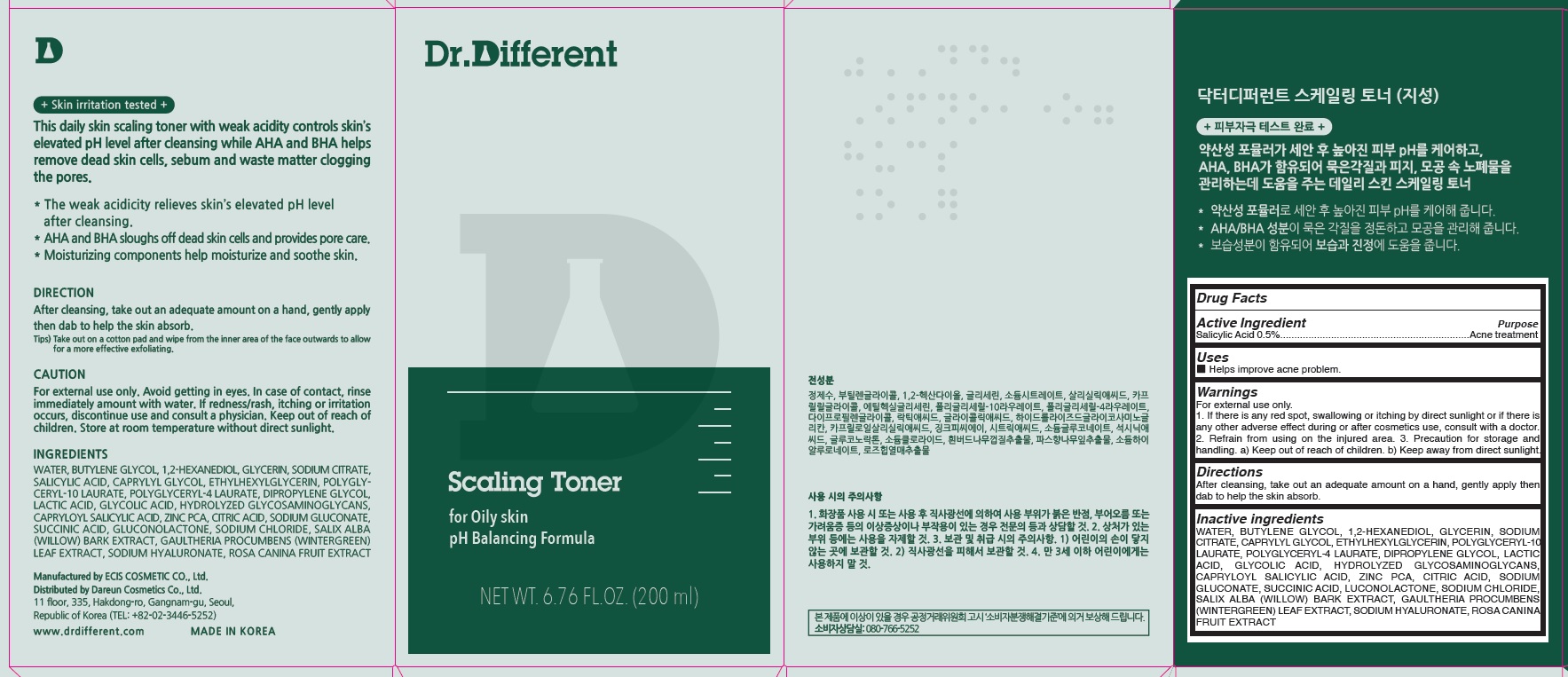 DRUG LABEL: Dr.Different Scaling Toner for Oily skin
NDC: 81710-010 | Form: LIQUID
Manufacturer: Dareun Cosmetics Co., Ltd.
Category: otc | Type: HUMAN OTC DRUG LABEL
Date: 20210409

ACTIVE INGREDIENTS: Salicylic Acid 0.5 g/100 mL
INACTIVE INGREDIENTS: WATER; BUTYLENE GLYCOL; 1,2-HEXANEDIOL

ACTIVE INGREDIENT

Salicylic Acid 0.5%

INACTIVE INGREDIENTS

WATER, BUTYLENE GLYCOL, 1,2-HEXANEDIOL, GLYCERIN, SODIUM CITRATE, CAPRYLYL GLYCOL, ETHYLHEXYLGLYCERIN, POLYGLYCERYL-10 LAURATE, POLYGLYCERYL-4 LAURATE, DIPROPYLENE GLYCOL, LACTIC ACID, GLYCOLIC ACID, HYDROLYZED GLYCOSAMINOGLYCANS, CAPRYLOYL SALICYLIC ACID, ZINC PCA, CITRIC ACID, SODIUM GLUCONATE, SUCCINIC ACID, LUCONOLACTONE, SODIUM CHLORIDE, SALIX ALBA (WILLOW) BARK EXTRACT, GAULTHERIA PROCUMBENS (WINTERGREEN) LEAF EXTRACT, SODIUM HYALURONATE, ROSA CANINA FRUIT EXTRACT

PURPOSE

Acne treatment

WARNINGS

For external use only.
1. If there is any red spot, swallowing or itching by direct sunlight or if there is any other adverse effect during or after cosmetics use, consult with a doctor.
2. Refrain from using on the injured area.
3. Precaution for storage and handling.
a) Keep out of reach of children.
b) Keep away from direct sunlight.

KEEP OUT OF REACH OF CHILDREN

Uses

■ Helps improve acne problem.

Directions

■ After cleansing, take out an adequate amount on a hand, gently apply then dab to help the skin absorb.